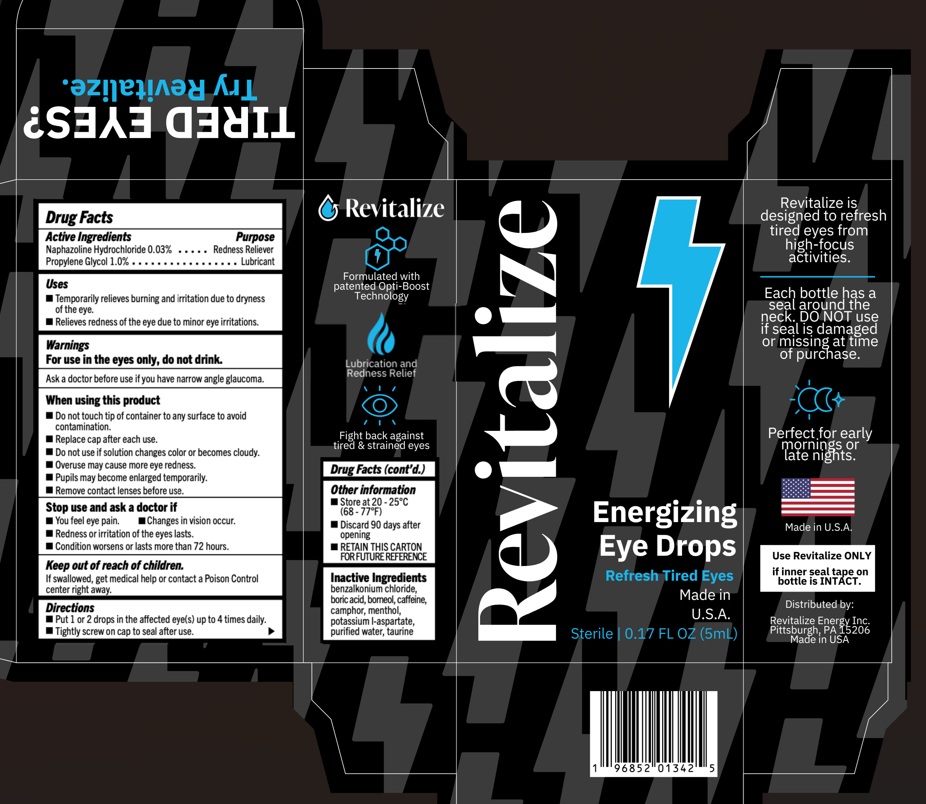 DRUG LABEL: Revitalize Energizing Eye Drops
NDC: 82864-001 | Form: LIQUID
Manufacturer: Revitalize Energy Inc.
Category: otc | Type: HUMAN OTC DRUG LABEL
Date: 20250731

ACTIVE INGREDIENTS: NAPHAZOLINE HYDROCHLORIDE 0.03 g/100 mL; PROPYLENE GLYCOL 1 g/100 mL
INACTIVE INGREDIENTS: BENZALKONIUM CHLORIDE; BORIC ACID; BORNEOL; CAFFEINE; CAMPHOR (SYNTHETIC); MENTHOL, UNSPECIFIED FORM; POTASSIUM ASPARTATE; WATER; TAURINE

Drug Facts

Active Ingredient Purpose

Naphozoline Hydrochloride 0.03% Redness Reliver
Propylene Glycol 1.0% Lubricant

Uses

- Temporarily relieves burning and irritation due to dryness of the eye
- Relieves redness of the eye due to minor eye irritations

Warnings

For external use only

For use in the eyes only, do not drink

Ask a doctor before use if you have narrow angle glaucoma

When using this product

• Do not touch tip of container to any surface to avoid contamination
• Replace each cap after each use
• Do not use if solution changes color or becomes cloudy
• Overuse may cause more eye redness
• Pupils may become enlarged temporarily
• Remove contact lenses before use

Stop Use and ask a doctor if
• You feel eye pain
• Changes in vision occur
• Redness or irritation of the eyes lasts
• Condition worsens or lasts more than 72 hours

Keep out of reach of children
• If swallowed, get medical help or contact a Poison Control center right away

Directions

Put 1 or 2 drops in the affected eye(s) up to 4 times daily
Tightly screw on cap to seal after use

Other information

Store at 20 - 25°C (68 -77°F)

Inactive ingredients

Benzalkonium Chloride, Boric Acid, Borneol, Caffeine, Camphor, menthol, potassium l-aspartate, purified water, Taurine